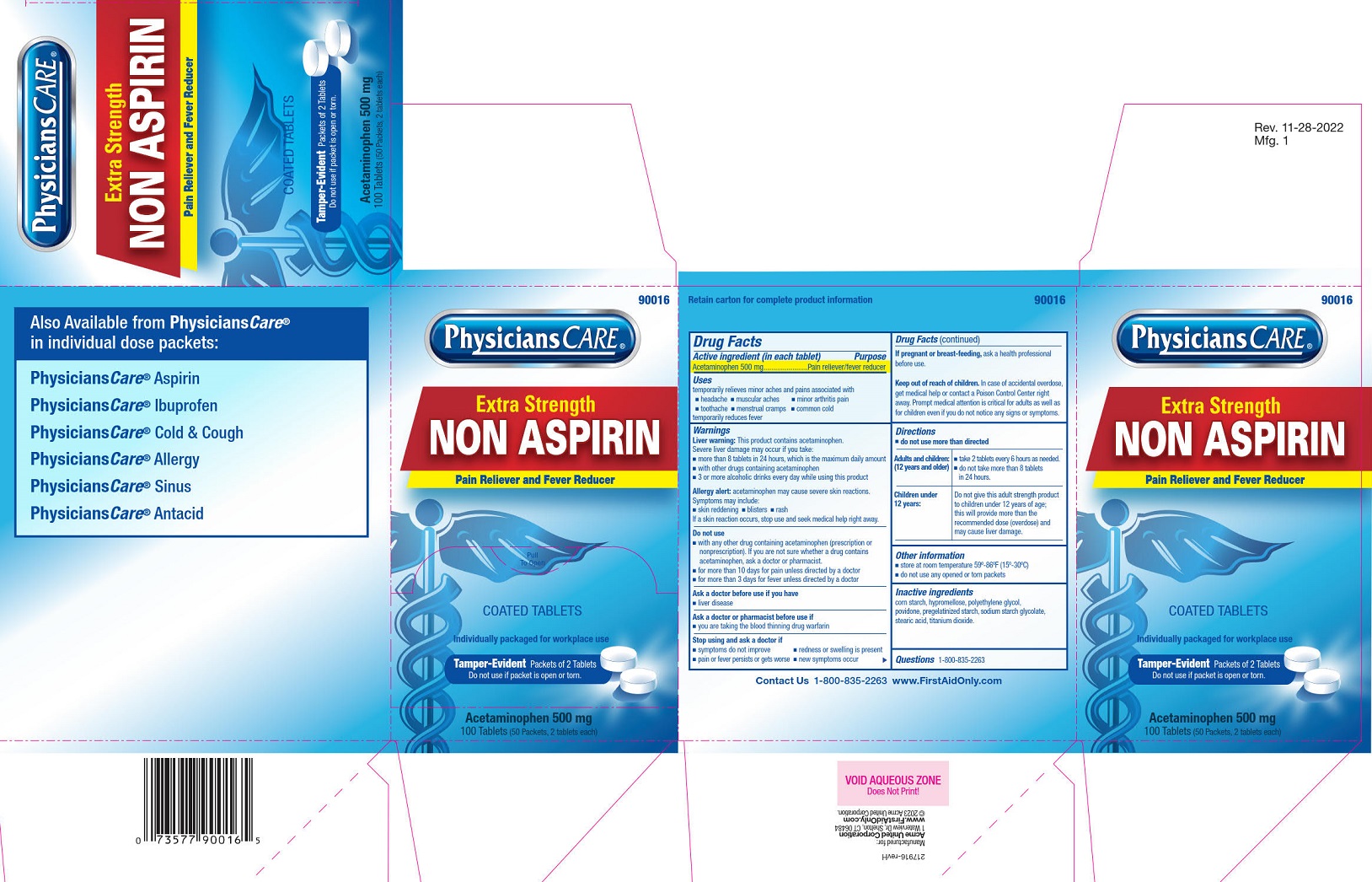 DRUG LABEL: PhysiciansCare Non Aspirin
NDC: 0924-0123 | Form: TABLET, FILM COATED
Manufacturer: Acme United Corporation
Category: otc | Type: HUMAN OTC DRUG LABEL
Date: 20251031

ACTIVE INGREDIENTS: ACETAMINOPHEN 500 mg/1 1
INACTIVE INGREDIENTS: HYPROMELLOSES; POVIDONE; SODIUM STARCH GLYCOLATE TYPE A POTATO; STARCH, CORN; STEARIC ACID; TITANIUM DIOXIDE; POLYETHYLENE GLYCOL, UNSPECIFIED

PhysiciansCare Non Aspirin Extra Strength (Acetaminophen)

Drug Facts

Active ingredient (in each tablet)

Acetaminophen 500 mg

Purpose

Pain reliever/fever reducer

Uses

temporarily relieves minor aches and pains associated with

■ headache

■ muscular aches

■ minor arthritis pain

■ toothache

■ menstrual cramps

■ common cold

temporarily reduces fever

WARNINGS

Liver warning: This product contains acetaminophen. Severe liver damage may occur if you take:

■ more than 8 tablets in 24 hours, which is the maximum daily amount

■ with other drugs containing acetaminophen

■ 3 or more alcoholic drinks every day while using this product

Allergy alert: Acetaminophen may cause severe skin reactions. Symptoms may include:

■ skin reddening

■ blisters

■ rash

If a skin reaction occurs, stop use and seek medical help right away.

Do not use

■ with any other drug containing acetaminophen (prescription or nonprescription). If you are not sure whether a
drug contains acetaminophen, ask a doctor or pharmacist.

■ for more than 10 days for pain unless directed by a doctor

■ for more than 3 days for fever unless directed by a doctor

Ask a doctor before use if you have

■ liver disease

Ask a doctor or pharmacist before use if

■ you are taking the blood thinning drug warfarin

Stop use and ask a doctor if

■ symptoms do not improve

■ redness or swelling is present

■ pain or fever persists or gets worse

■ new symptoms occur

PREGNANCY OR BREAST FEEDING

If pregnant or breast-feeding, ask a health professional before use.

Keep out of reach of children. In case of accidental overdose, get medical help or contact a Poison Control Center right away. Prompt medical attention is critical for adults as well as for children even if you do not notice any signs or symptoms.

Directions

■ do not use more than directed

Adults and children: (12 years and older)

- take 2 tablets every 6 hours as needed.
- do not take more than 8 tablets in 24 hours.

Children under 12 years: Do not give this adult strength product to children under 12 years of age; this will provide more than the recommended dose (overdose) and may cause liver damage.

Other information

■ store at room temperature 59º-86ºF (15º-30ºC)

■ do not use any opened or torn packets

Inactive ingredients

corn starch, hypromellose, polyethylene glycol, povidone, pregelatinized starch, sodium starch glycolate, stearic acid, titanium dioxide.

Questions? 1-800-835-2263

PhysiciansCare XS Non Aspirin Label

Physicians Care®

Extra Strength Non Aspirin

Pain Reliever and Fever Reducer

Pull To Open

Coated Tablets

Individually packaged for workplace use

Tamper-Evident Packets of 2 Tablets

Do not use if packet is open or torn.

Aceatminiphen 500 mg

100 Tablets (50 Packets, 2 tablets each)

90016